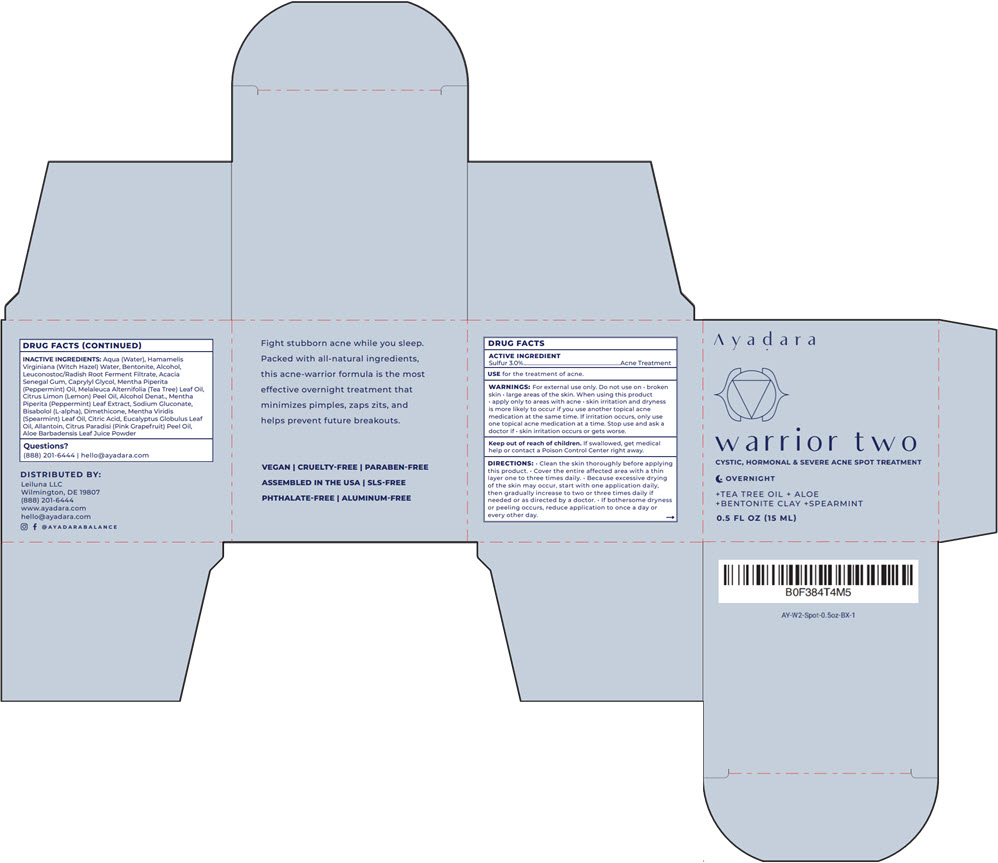 DRUG LABEL: Ayadara Cystic Acne Spot Treatment
NDC: 72841-206 | Form: PASTE
Manufacturer: Leiluna LLC
Category: otc | Type: HUMAN OTC DRUG LABEL
Date: 20251125

ACTIVE INGREDIENTS: SULFUR 30 mg/1 mL
INACTIVE INGREDIENTS: WATER; HAMAMELIS VIRGINIANA TOP WATER; BENTONITE; ALCOHOL; LEUCONOSTOC/RADISH ROOT FERMENT FILTRATE; ACACIA; CAPRYLYL GLYCOL; PEPPERMINT OIL; TEA TREE OIL; LEMON OIL, COLD PRESSED; MENTHA PIPERITA LEAF; LEVOMENOL; SODIUM GLUCONATE; DIMETHICONE; SPEARMINT OIL; CITRIC ACID MONOHYDRATE; EUCALYPTUS OIL; ALLANTOIN; GRAPEFRUIT OIL; ALOE VERA LEAF

Ayadara Cystic Acne Spot Treatment

DRUG FACTS

ACTIVE INGREDIENT

Sulfur 3.0%

PURPOSE

Acne Treatment

USE

for the treatment of acne.

WARNINGS

For external use only.

Do not use on

- broken skin
- large areas of the skin.

When using this product

- apply only to areas with acne
- skin irritation and dryness is more likely to occur if you use another topical acne medication at the same time. If irritation occurs, only use one topical acne medication at a time.

Stop use and ask a doctor if

- skin irritation occurs or gets worse.

Keep out of reach of children. If swallowed, get medical help or contact a Poison Control Center right away.

DIRECTIONS

- Clean the skin thoroughly before applying this product.
- Cover the entire affected area with a thin layer one to three times daily.
- Because excessive drying of the skin may occur, start with one application daily, then gradually increase to two or three times daily if needed or as directed by a doctor.
- If bothersome dryness or peeling occurs, reduce application to once a day or every other day.

INACTIVE INGREDIENTS

Aqua (Water), Hamamelis Virginiana (Witch Hazel) Water, Bentonite, Alcohol, Leuconostoc/Radish Root Ferment Filtrate, Acacia Senegal Gum, Caprylyl Glycol, Mentha Piperita (Peppermint) Oil, Melaleuca Alternifolia (Tea Tree) Leaf Oil, Citrus Limon (Lemon) Peel Oil, Alcohol Denat., Mentha Piperita (Peppermint) Leaf Extract, Sodium Gluconate, Bisabolol (L-alpha), Dimethicone, Mentha Viridis (Spearmint) Leaf Oil, Citric Acid, Eucalyptus Globulus Leaf Oil, Allantoin, Citrus Paradisi (Pink Grapefruit) Peel Oil, Aloe Barbadensis Leaf Juice Powder

Questions?

(888) 201-6444 | hello@ayadara.com

DISTRIBUTED BY:
Leiluna LLC
Wilmington, DE 19807

PRINCIPAL DISPLAY PANEL - 15 ML Jar Box

Ayadara

warrior two
CYSTIC, HORMONAL & SEVERE ACNE SPOT TREATMENT

OVERNIGHT

+TEA TREE OIL + ALOE
+BENTONITE CLAY +SPEARMINT

0.5 FL OZ (15 ML)